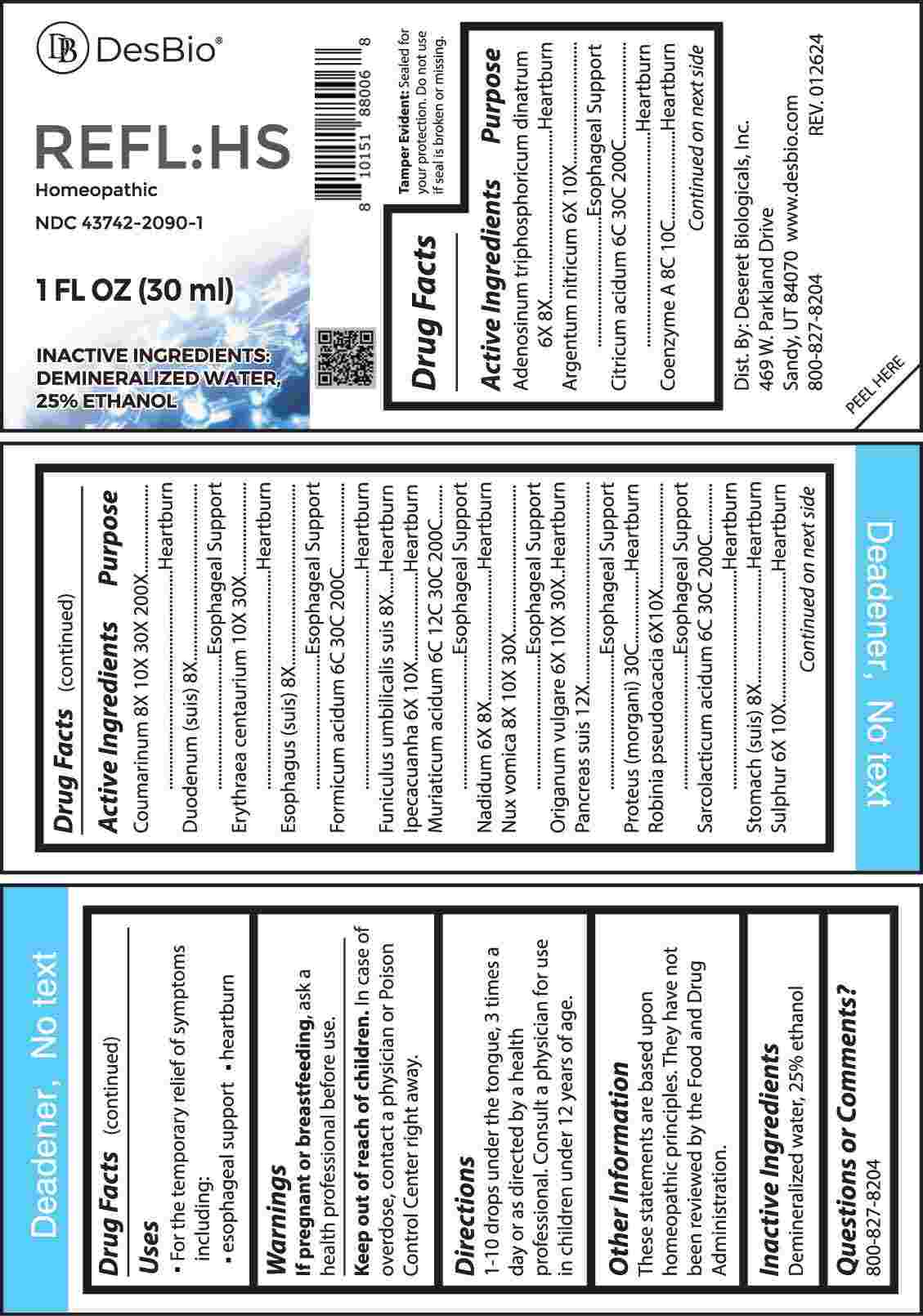 DRUG LABEL: REFL HS
NDC: 43742-2090 | Form: LIQUID
Manufacturer: Deseret Biologicals, Inc.
Category: homeopathic | Type: HUMAN OTC DRUG LABEL
Date: 20240429

ACTIVE INGREDIENTS: ADENOSINE TRIPHOSPHATE DISODIUM 6 [hp_X]/1 mL; NADIDE 6 [hp_X]/1 mL; SILVER NITRATE 6 [hp_X]/1 mL; IPECAC 6 [hp_X]/1 mL; ROBINIA PSEUDOACACIA BARK 6 [hp_X]/1 mL; SULFUR 6 [hp_X]/1 mL; OREGANO 6 [hp_X]/1 mL; SUS SCROFA DUODENUM 8 [hp_X]/1 mL; SUS SCROFA ESOPHAGUS 8 [hp_X]/1 mL; SUS SCROFA UMBILICAL CORD 8 [hp_X]/1 mL; SUS SCROFA STOMACH 8 [hp_X]/1 mL; STRYCHNOS NUX-VOMICA SEED 8 [hp_X]/1 mL; COUMARIN 8 [hp_X]/1 mL; CENTAURIUM ERYTHRAEA 10 [hp_X]/1 mL; SUS SCROFA PANCREAS 12 [hp_X]/1 mL; HYDROCHLORIC ACID 6 [hp_C]/1 mL; ANHYDROUS CITRIC ACID 6 [hp_C]/1 mL; FORMIC ACID 6 [hp_C]/1 mL; LACTIC ACID, L- 6 [hp_C]/1 mL; COENZYME A 8 [hp_C]/1 mL; PROTEUS INCONSTANS 30 [hp_C]/1 mL
INACTIVE INGREDIENTS: WATER; ALCOHOL

DRUG FACTS:

ACTIVE INGREDIENTS:

Adenosinum Triphosphoricum Dinatrum 6X, 8X, Argentum Nitricum 6X, 10X, Citricum Acidum 6C, 30C, 200C, Coenzyme A 8C, 10C, Coumarinum 8X, 10X, 30X, 200X, Duodenum (Suis) 8X, Erythraea Centaurium 10X, 30X, Esophagus (Suis) 8X, Formicum Acidum 6C, 30C, 200C, Funiculus Umbilicalis Suis 8X, Ipecacuanha 6X, 10X, Muriaticum Acidum 6C, 12C, 30C, 200C, Nadidum 6X, 8X, Nux Vomica 8X, 10X, 30X, Origanum Vulgare 6X, 10X, 30X, Pancreas (Suis) 12X, Proteus (Morgani) 30C, Robinia Pseudoacacia 6X, 10X, Sarcolacticum Acidum 6C, 30C, 200C, Stomach (Suis) 8X, Sulphur 6X, 10X.

PURPOSE:

Adenosinum Triphosphoricum Dinatrum - Heartburn, Argentum Nitricum – Esophageal Support, Citricum Acidum - Heartburn, Coenzyme A - Heartburn, Coumarinum - Heartburn, Duodenum (Suis) – Esophageal Support, Erythraea Centaurium - Heartburn, Esophagus (Suis) – Esophageal Support, Formicum Acidum - Heartburn, Funiculus Umbilicalis Suis - Heartburn, Ipecacuanha - Heartburn, Muriaticum Acidum – Esophageal Support, Nadidum - Heartburn, Nux Vomica – Esophageal Support, Origanum Vulgare - Heartburn, Pancreas (Suis) – Esophageal Support, Proteus (Morgani) - Heartburn, Robinia Pseudoacacia – Esophageal Support, Sarcolacticum Acidum - Heartburn, Stomach (Suis) - Heartburn, Sulphur - Heartburn

USES:

• For the temporary relief of symptoms including:

• esophageal support • heartburn

These statements are based upon homeopathic principles. They have not been reviewed by the Food and Drug Administration.

WARNINGS:

If pregnant or breast-feeding, ask a health professional before use.

Keep out of reach of children. In case of overdose, contact a physician or Poison Control Center right away.

Tamper Evident: Sealed for your protection. Do not use if seal is broken or missing.

KEEP OUT OF REACH OF CHILDREN:

In case of overdose, contact a physician or Poison Control Center right away.

DIRECTIONS:

1-10 drops under the tongue, 3 times a day or as directed by a health professional. Consult a physician for use in children under 12 years of age.

INACTIVE INGREDIENTS:

Demineralized water, 25% ethanol

QUESTIONS:

Dist. By: Deseret Biologicals, Inc.
469 W. Parkland Drive
Sandy, UT 84070

www.desbio.com

800-827-8204

PACKAGE LABEL DISPLAY:

Des Bio

REFL:HS

Homeopathic

NDC 43742-2090-1

1 FL OZ (30 ml)